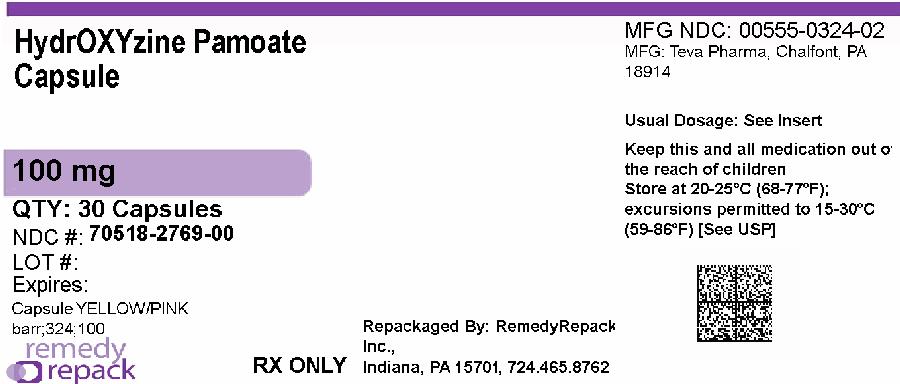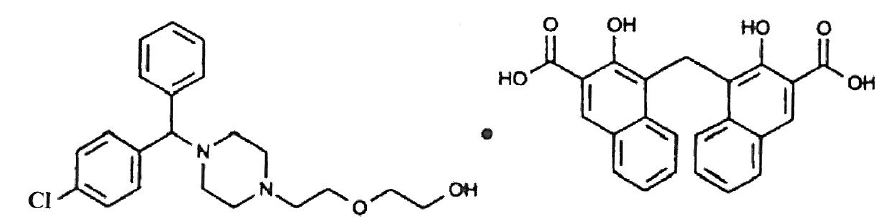 DRUG LABEL: Hydroxyzine Pamoate
NDC: 70518-2769 | Form: CAPSULE
Manufacturer: REMEDYREPACK INC.
Category: prescription | Type: HUMAN PRESCRIPTION DRUG LABEL
Date: 20260211

ACTIVE INGREDIENTS: HYDROXYZINE PAMOATE 100 mg/1 1
INACTIVE INGREDIENTS: CROSCARMELLOSE SODIUM; MAGNESIUM STEARATE; STARCH, CORN; LACTOSE MONOHYDRATE; D&C RED NO. 28; D&C RED NO. 33; D&C YELLOW NO. 10; FD&C BLUE NO. 1; FD&C RED NO. 40; GELATIN; TITANIUM DIOXIDE; FERROSOFERRIC OXIDE; FD&C BLUE NO. 2; INDIGOTINDISULFONATE SODIUM; PROPYLENE GLYCOL; SHELLAC

HydrOXYzine Pamoate Capsules, USP

Rx only

DESCRIPTION

Hydroxyzine pamoate, USP is designated chemically as 1-(p-chlorobenzhydryl) 4-[2-(2-hydroxyethoxy) ethyl] diethylenediamine salt of 1,1′-methylene bis (2 hydroxy-3-naphthalene carboxylic acid). It has the following structural formula:

C21H27ClN2O2•C23H16O6 M.W. 763.27

Hydroxyzine pamoate capsules, USP are administered in doses equivalent to 25 mg, 50 mg or 100 mg of hydroxyzine hydrochloride. In addition, each capsule contains the following inactive ingredients: croscarmellose sodium, magnesium stearate, and pregelatinized corn starch. The 25 mg also contains anhydrous lactose. The 50 mg and 100 mg also contain lactose monohydrate. The capsule shell ingredients for the 25 mg capsule are D&C Red No. 28, D&C Yellow No. 10, FD&C Blue No. 1, FD&C Red No. 40, FD&C Yellow No. 6, gelatin, and titanium dioxide. The 50 mg capsule shell contains D&C Red No. 33, D&C Yellow No. 10, FD&C Yellow No. 6, gelatin, and titanium dioxide. The 100 mg capsule shell contains D&C Red No. 28, D&C Red No. 33, D&C Yellow No. 10, FD&C Blue No. 1, FD&C Red No. 40, gelatin, and titanium dioxide.

The edible imprinting ink on the 25 mg, 50 mg and 100 mg capsules contains black iron oxide, D&C Yellow No. 10 aluminum lake, FD&C Blue No. 1 aluminum lake, FD&C Blue No. 2 aluminum lake, FD&C Red No. 40 aluminum lake, propylene glycol, and shellac glaze.

CLINICAL PHARMACOLOGY

Hydroxyzine pamoate is unrelated chemically to the phenothiazines, reserpine, meprobamate, or the benzodiazepines.

Hydroxyzine pamoate is not a cortical depressant, but its action may be due to a suppression of activity in certain key regions of the subcortical area of the central nervous system. Primary skeletal muscle relaxation has been demonstrated experimentally. Bronchodilator activity, and antihistaminic and analgesic effects have been demonstrated experimentally and confirmed clinically. An antiemetic effect, both by the apomorphine test and the veriloid test, has been demonstrated. Pharmacological and clinical studies indicate that hydroxyzine in therapeutic dosage does not increase gastric secretion or acidity and in most cases has mild antisecretory activity. Hydroxyzine is rapidly absorbed from the gastrointestinal tract and hydroxyzine pamoate's clinical effects are usually noted within 15 to 30 minutes after oral administration.

INDICATIONS AND USAGE

For symptomatic relief of anxiety and tension associated with psychoneurosis and as an adjunct in organic disease states in which anxiety is manifested.

Useful in the management of pruritus due to allergic conditions such as chronic urticaria and atopic and contact dermatoses, and in histamine-mediated pruritus.

As a sedative when used as premedication and following general anesthesia, hydroxyzine may potentiate meperidine (Demerol®) and barbiturates , so their use in pre-anesthetic adjunctive therapy should be modified on an individual basis. Atropine and other belladonna alkaloids are not affected by the drug. Hydroxyzine is not known to interfere with the action of digitalis in any way and it may be used concurrently with this agent.

The effectiveness of hydroxyzine as an antianxiety agent for long-term use, that is, more than 4 months, has not been assessed by systematic clinical studies. The physician should reassess periodically the usefulness of the drug for the individual patient.

CONTRAINDICATIONS

Hydroxyzine, when administered to the pregnant mouse, rat, and rabbit, induced fetal abnormalities in the rat and mouse at doses substantially above the human therapeutic range. Clinical data in human beings are inadequate to establish safety in early pregnancy. Until such data are available, hydroxyzine is contraindicated in early pregnancy.

Hydroxyzine is contraindicated in patients with a prolonged QT interval.

Hydroxyzine pamoate is contraindicated for patients who have shown a previous hypersensitivity to any component of this medication.

Hydroxyzine is contraindicated in patients with known hypersensitivity to hydroxyzine products, and in patients with known hypersensitivity to cetirizine hydrochloride or levocetirizine hydrochloride.

WARNINGS

Nursing Mothers

It is not known whether this drug is excreted in human milk. Since many drugs are so excreted, hydroxyzine should not be given to nursing mothers.

PRECAUTIONS

THE POTENTIATING ACTION OF HYDROXYZINE MUST BE CONSIDERED WHEN THE DRUG IS USED IN CONJUNCTION WITH CENTRAL NERVOUS SYSTEM DEPRESSANTS SUCH AS NARCOTICS, NON-NARCOTIC ANALGESICS AND BARBITURATES. Therefore, when central nervous system depressants are administered concomitantly with hydroxyzine, their dosage should be reduced. Since drowsiness may occur with use of the drug, patients should be warned of this possibility and cautioned against driving a car or operating dangerous machinery while taking hydroxyzine pamoate. Patients should be advised against the simultaneous use of other CNS depressant drugs, and cautioned that the effect of alcohol may be increased.

QT Prolongation/Torsade de Pointes (TdP)

Cases of QT prolongation and Torsade de Pointes have been reported during postmarketing use of hydroxyzine. The majority of reports occurred in patients with other risk factors for QT prolongation/TdP (pre-existing heart disease, electrolyte imbalances or concomitant arrhythmogenic drug use). Therefore, hydroxyzine should be used with caution in patients with risk factors for QT prolongation, congenital long QT syndrome, a family history of long QT syndrome, other conditions that predispose to QT prolongation and ventricular arrhythmia, as well as recent myocardial infarction, uncompensated heart failure, and bradyarrhythmias.

Caution is recommended during the concomitant use of drugs known to prolong the QT interval. These include Class 1A (e.g., quinidine, procainamide) or Class III (e.g., amiodarone, sotalol) antiarrhythmics, certain antipsychotics (e.g., ziprasidone, iloperidone, clozapine, quetiapine, chlorpromazine), certain antidepressants (e.g., citalopram, fluoxetine), certain antibiotics (e.g., azithromycin, erythromycin, clarithromycin, gatifloxacin, moxifloxacin); and others (e.g., pentamidine, methadone, ondansetron, droperidol).

Acute Generalized Exanthematous Pustulosis (AGEP)

Hydroxyzine may rarely cause acute generalized exanthematous pustulosis (AGEP), a serious skin reaction characterized by fever and numerous small, superficial, non-follicular, sterile pustules, arising within large areas of edematous erythema. Inform patients about the signs of AGEP, and discontinue hydroxyzine at the first appearance of a skin rash, worsening of pre-existing skin reactions which hydroxyzine may be used to treat, or any other sign of hypersensitivity. If signs or symptoms suggest AGEP, use of hydroxyzine should not be resumed and alternative therapy should be considered. Avoid cetirizine or levocetirizine in patients who have experienced AGEP or other hypersensitivity reactions with hydroxyzine, due to the risk of cross-sensitivity.

Geriatric Use

A determination has not been made whether controlled clinical studies of hydroxyzine pamoate included sufficient numbers of subjects aged 65 and over to define a difference in response from younger subjects. Other reported clinical experience has not identified differences in responses between the elderly and younger patients. In general, dose selection for an elderly patient should be cautious, usually starting at the low end of the dosing range, reflecting the greater frequency of decreased hepatic, renal or cardiac function and of concomitant disease or other drug therapy.

The extent of renal excretion of hydroxyzine pamoate has not been determined. Because elderly patients are more likely to have decreased renal function, care should be taken in dose selections.

Sedating drugs may cause confusion and over sedation in the elderly; elderly patients generally should be started on low doses of hydroxyzine pamoate and observed closely.

ADVERSE REACTIONS

Side effects reported with the administration of hydroxyzine pamoate are usually mild and transitory in nature.

Skin and Appendages

Oral hydroxyzine hydrochloride is associated with Acute Generalized Exanthematous Pustulosis (AGEP) and fixed drug eruptions in postmarketing reports.

Anticholinergic

Dry mouth.

Central Nervous System

Drowsiness is usually transitory and may disappear in a few days of continued therapy or upon reduction of the dose. Involuntary motor activity, including rare instances of tremor and convulsions, has been reported, usually with doses considerably higher than those recommended. Clinically significant respiratory depression has not been reported at recommended doses.

Cardiac System

QT prolongation, Torsade de Pointes.

In postmarketing experience, the following additional undesirable effects have been reported:

Body as a Whole

allergic reaction.

Nervous System

headache.

Psychiatric

hallucination.

Skin and Appendages

pruritus, rash, urticaria.

To report SUSPECTED ADVERSE REACTIONS, contact Teva at 1-888-838-2872 or FDA at 1-800-FDA-1088 or www.fda.gov/medwatch.

OVERDOSAGE

The most common manifestation of overdosage of hydroxyzine pamoate is hypersedation. Other reported signs and symptoms were convulsions, stupor, nausea and vomiting. As in the management of overdosage with any drug, it should be borne in mind that multiple agents may have been taken.

If vomiting has not occurred spontaneously, it should be induced. Immediate gastric lavage is also recommended. General supportive care, including frequent monitoring of the vital signs and close observation of the patient, is indicated. Hypotension, though unlikely, may be controlled with intravenous fluids and vasopressors (do not use epinephrine as hydroxyzine counteracts its pressor action). Caffeine and Sodium Benzoate Injection, USP, may be used to counteract central nervous system depressant effects.

Hydroxyzine overdose may cause QT prolongation and Torsade de Pointes. ECG monitoring is recommended in cases of hydroxyzine overdose.

There is no specific antidote. It is doubtful that hemodialysis would be of any value in the treatment of overdosage with hydroxyzine. However, if other agents such as barbiturates have been ingested concomitantly, hemodialysis may be indicated. There is no practical method to quantitate hydroxyzine in body fluids or tissue after its ingestion or administration.

DOSAGE AND ADMINISTRATION

For symptomatic relief of anxiety and tension associated with psychoneurosis and as an adjunct in organic disease states in which anxiety is manifested: in adults, 50 to 100 mg four times a day; children under 6 years, 50 mg daily in divided doses; and over 6 years, 50 to 100 mg daily in divided doses.

For use in the management of pruritus due to allergic conditions such as chronic urticaria and atopic and contact dermatoses, and in histamine-mediated pruritus: in adults, 25 mg three times a day or four times a day.; children under 6 years, 50 mg daily in divided doses; and over 6 years, 50 to 100 mg daily in divided doses.

As a sedative when used as a premedication and following general anesthesia: 50 to 100 mg in adults, and 0.6 mg/kg in children.

When treatment is initiated by the intramuscular route of administration, subsequent doses may be administered orally.

As with all medications, the dosage should be adjusted according to the patient’s response to therapy.

HOW SUPPLIED

Hydroxyzine pamoate capsules, USP (hydroxyzine pamoate, USP equivalent to hydroxyzine hydrochloride), 100 mg are available as light yellow opaque cap and pink opaque body filled with yellow powder, imprinted in black ink stylized “barr” over “324” on one piece and “100” on the other piece, packaged in

NDC: 70518-2769-00

PACKAGING: 30 in 1 BLISTER PACK

Dispense in a tight, light-resistant container as defined in the USP, with a child-resistant closure (as required).

Store at 20° to 25°C (68° to 77°F) [See USP Controlled Room Temperature].

Keep this and all medications out of the reach of children.

Repackaged and Distributed By:

Remedy Repack, Inc.

625 Kolter Dr. Suite #4 Indiana, PA 1-724-465-8762

PACKAGE LABEL

DRUG: Hydroxyzine Pamoate

GENERIC: Hydroxyzine Pamoate

DOSAGE: CAPSULE

ADMINSTRATION: ORAL

NDC: 70518-2769-0

COLOR: yellow

SHAPE: CAPSULE

SCORE: No score

SIZE: 19 mm

IMPRINT: barr;324;100

PACKAGING: 30 in 1 BLISTER PACK

ACTIVE INGREDIENT(S):

- HYDROXYZINE PAMOATE 100mg in 1

INACTIVE INGREDIENT(S):

- CROSCARMELLOSE SODIUM
- MAGNESIUM STEARATE
- STARCH, CORN
- LACTOSE MONOHYDRATE
- D&C RED NO. 28
- D&C RED NO. 33
- D&C YELLOW NO. 10
- FD&C BLUE NO. 1
- FD&C RED NO. 40
- GELATIN
- TITANIUM DIOXIDE
- FERROSOFERRIC OXIDE
- FD&C BLUE NO. 2
- INDIGOTINDISULFONATE SODIUM
- PROPYLENE GLYCOL
- SHELLAC